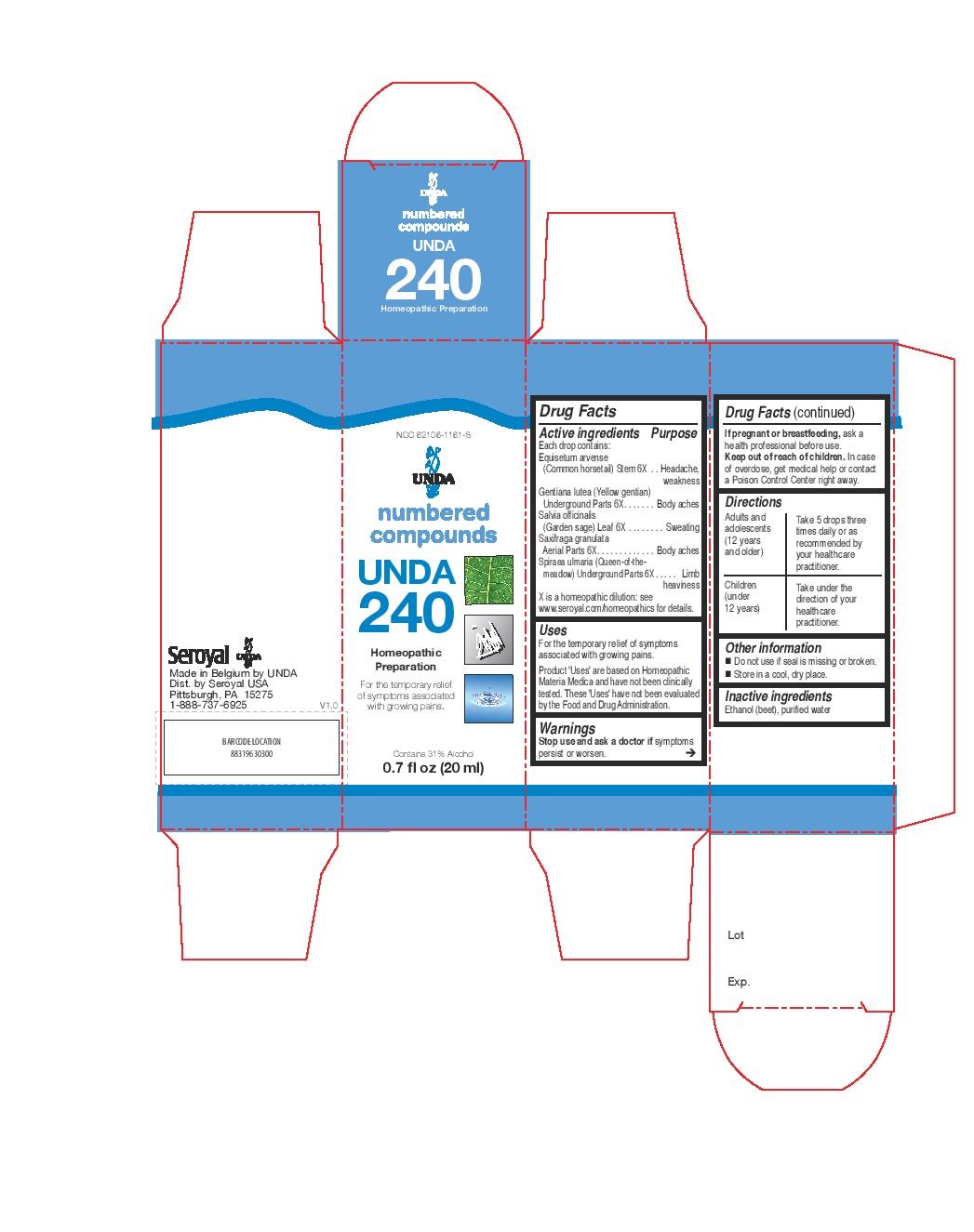 DRUG LABEL: UNDA 240
NDC: 62106-1161 | Form: LIQUID
Manufacturer: Seroyal USA
Category: homeopathic | Type: HUMAN OTC DRUG LABEL
Date: 20221109

ACTIVE INGREDIENTS: FILIPENDULA ULMARIA ROOT 6 [hp_X]/20 mL; SAGE 6 [hp_X]/20 mL; GENTIANA LUTEA ROOT 6 [hp_X]/20 mL; SAXIFRAGA GRANULATA FLOWERING TOP 6 [hp_X]/20 mL; EQUISETUM ARVENSE BRANCH 6 [hp_X]/20 mL
INACTIVE INGREDIENTS: ALCOHOL; WATER

UNDA 240

Active ingredients
Each drop contains:
Equisetum arvense (Common horsetail) Stem 6X
Gentiana lutea (Yellow gentian) Underground Parts 6X
Salvia officinalis (Garden sage) Leaf 6X
Saxifraga granulata Aerial Parts 6X
Spiraea ulmaria (Queen-of-themeadow) Underground Parts 6X

Uses
For the temporary relief of symptoms associated with growing pains.

Warnings
Stop use and ask a doctor if symptoms persist or worsen.

If pregnant or breastfeeding, ask a health professional before use.
Keep out of reach of children. In case of overdose, get medical help or contact a Poison Control Center right away.

Keep out of reach of children. In case of overdose, get medical help or contact a Poison Control Center right away.

PREGNANCY OR BREAST FEEDING

If pregnant or breastfeeding, ask a health professional before use.

Other information
Do not use if seal is missing or broken.
Store in a cool, dry place.

Inactive ingredients
Ethanol (beet), purified water

Directions
Adults and adolescents (12 years and older)

Take 5 drops three times daily or as recommended by your healthcare practitioner.

Children (under 12 years)

Take under the direction of your healthcare practitioner.

Uses
For the temporary relief of symptoms associated with growing pains.

Directions
Adults and adolescents (12 years and older)

Take 5 drops three times daily or as recommended by your healthcare practitioner.

Children (under 12 years)

Take under the direction of your healthcare practitioner.

PACKAGE LABEL

NDC 62106-1161-8

UNDA

numbered compounds

UNDA 240

Homeopathic Preparation

For the temporary relief of symptoms associated with growing pains.

Contains 31% Alcohol

0.7 fl oz (20 ml)